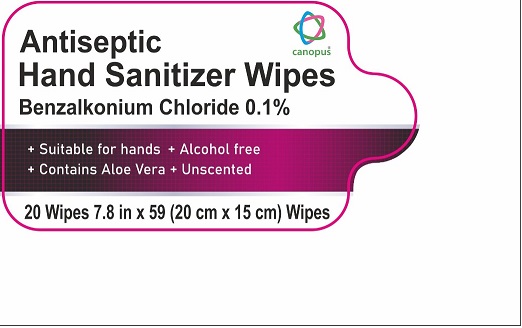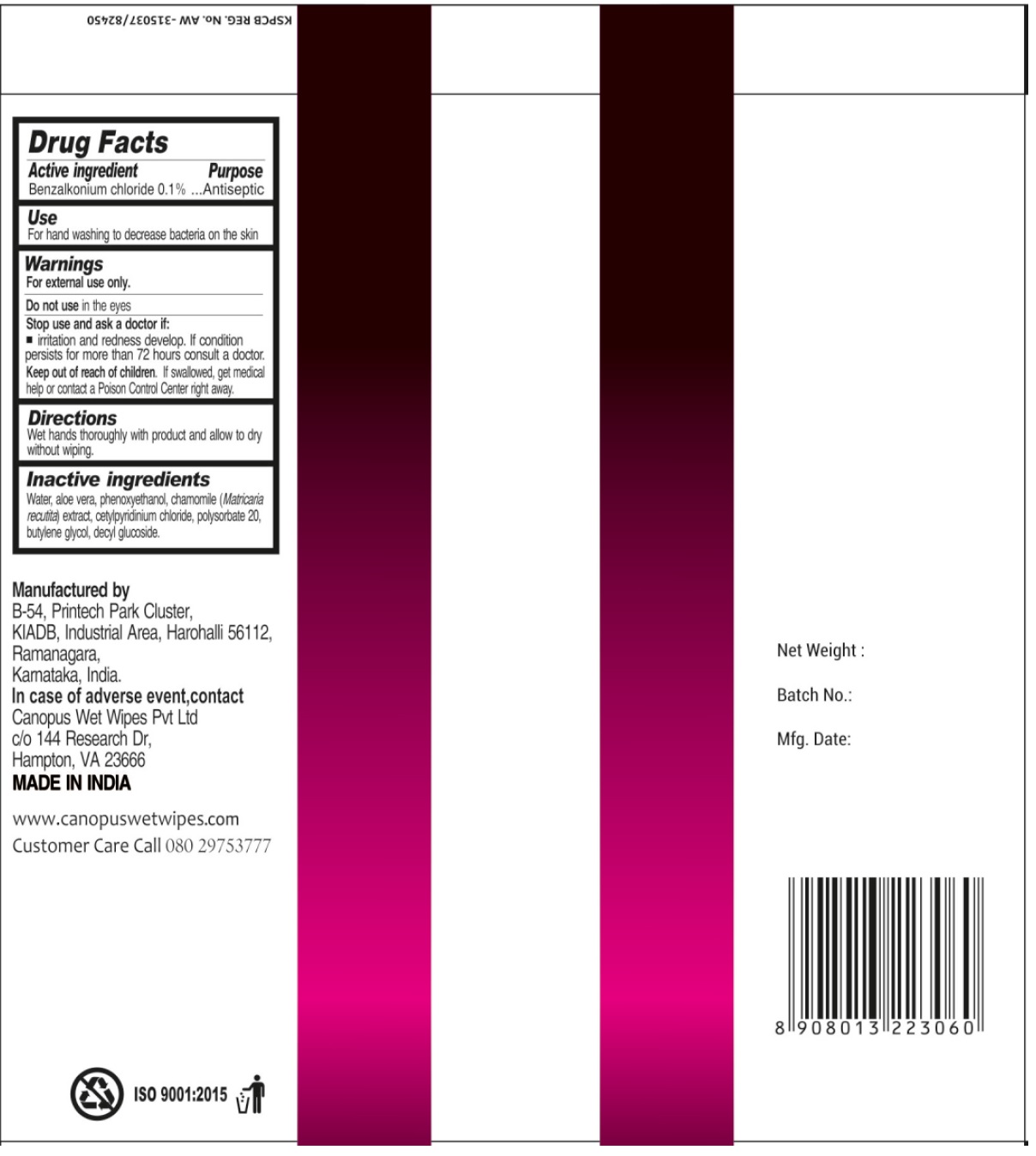 DRUG LABEL: Antiseptic Hand Sanitizer Wipes Benzalkonium Chloride
NDC: 81063-001 | Form: CLOTH
Manufacturer: CANOPUS WET WIPES PRIVATE LIMITED
Category: otc | Type: HUMAN OTC DRUG LABEL
Date: 20240116

ACTIVE INGREDIENTS: BENZALKONIUM CHLORIDE 1 mg/1 mL
INACTIVE INGREDIENTS: WATER; ALOE VERA LEAF; PHENOXYETHANOL; CHAMOMILE; CETYLPYRIDINIUM CHLORIDE; POLYSORBATE 20; BUTYLENE GLYCOL; DECYL GLUCOSIDE

Antiseptic Hand Sanitizer Wipes - Benzalkonium Chloride

Active ingredient

Benzalkonium chloride 0.1%

Purpose

Antiseptic

Use

For hand washing to decrease bacteria on ths skin

Warnings

For external use only.

Do not use

in the eyes.

Stop use and ask a doctor if:

irritation and redness develop. If condition persists for more than 72 hours consult a doctor.

Keep out of reach of children.

If swallowed, get medical help or contact Poison Control Centre right away.

Directions

Wet hands thoroughly with product and allow to dry without wiping.

Inactive ingredients

Water, aloe vera, phenoxyethanol, chamomile (Matricaria recutita) extract, cetylpyridinium chloride, polysorbate 20, butylene glycol, decyl glucoside.